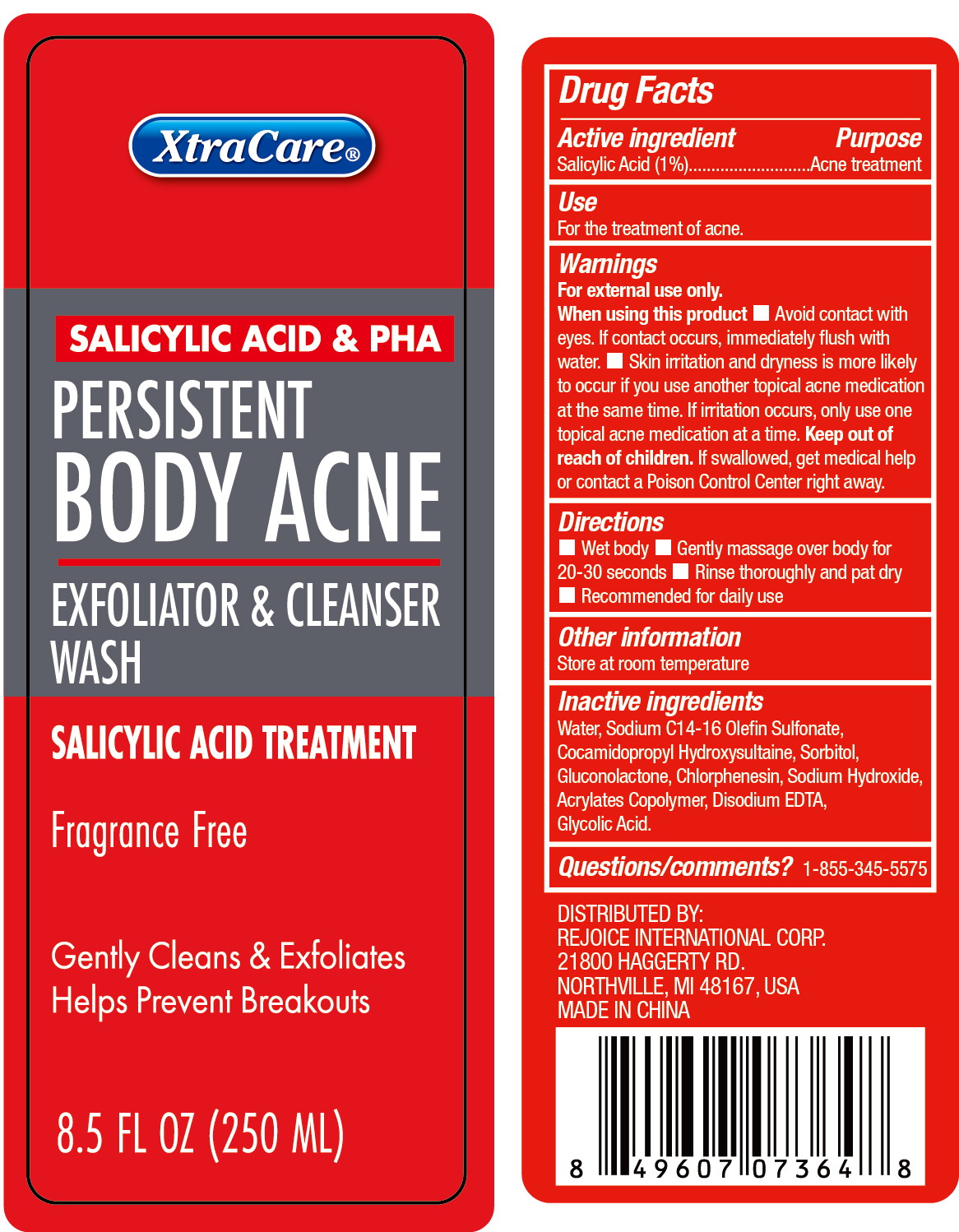 DRUG LABEL: PERSISTENT BODY ACNE WASH 8.5OZ
NDC: 58503-169 | Form: LIQUID
Manufacturer: China Ningbo Shangge Cosmetics Technology Corp.
Category: otc | Type: HUMAN OTC DRUG LABEL
Date: 20231009

ACTIVE INGREDIENTS: SALICYLIC ACID 1 mg/100 mL
INACTIVE INGREDIENTS: WATER; SODIUM HYDROXIDE; EDETATE DISODIUM ANHYDROUS; GLYCOLIC ACID; SODIUM C14-16 OLEFIN SULFONATE; SORBITOL; GLUCONOLACTONE; CHLORPHENESIN; COCAMIDOPROPYL HYDROXYSULTAINE; BUTYL ACRYLATE/METHYL METHACRYLATE/METHACRYLIC ACID COPOLYMER (18000 MW)

Active ingredient

Salicylic Acid (1%)

Purpose

Acne treatment

Use

For the treatment of acne.

Warnings

For external use only.

When using this product

- Avoid contact with eyes. If contact occurs, immediately fulsh with water.
- Skin irritation and dryness is more likely to occur if you use another topical ance medication at the same time. If irritation occurs, only use one topical acne medication at a time.

Keep out of reach of children

If swallowed, get medical help or contact a Poison Control Center right away.

Directions

- Wet body
- Gently massage over body for 20-30 seconds
- Rinse thoroughly and pat dry
- Recommended for daily use

Other information

Store at room temperature

Inactive ingredients

Water

Sodium C14-16 Olefin Sulfonate

Cocamidopropyl Hydroxysultaine

Sorbitol

Gluconolactone

Chlorphenesin

Sodium Hydroxide

Acrylates Copolymer

Disodium EDTA

Glycolic Acid